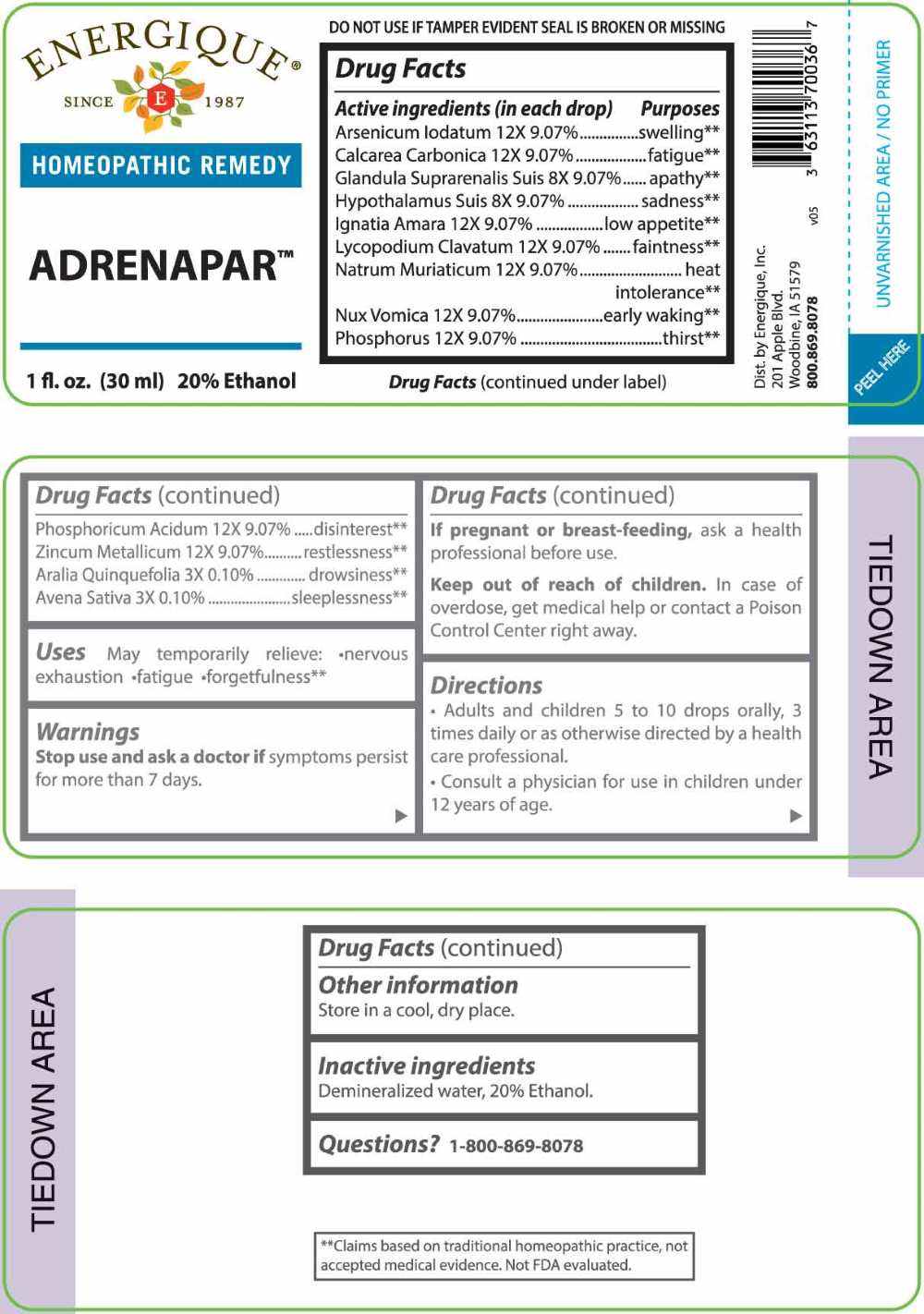 DRUG LABEL: Adrenapar
NDC: 44911-0715 | Form: LIQUID
Manufacturer: Energique, Inc.
Category: homeopathic | Type: HUMAN OTC DRUG LABEL
Date: 20240729

ACTIVE INGREDIENTS: AMERICAN GINSENG 3 [hp_X]/1 mL; AVENA SATIVA FLOWERING TOP 3 [hp_X]/1 mL; SUS SCROFA ADRENAL GLAND 8 [hp_X]/1 mL; SUS SCROFA HYPOTHALAMUS 8 [hp_X]/1 mL; ARSENIC TRIIODIDE 12 [hp_X]/1 mL; OYSTER SHELL CALCIUM CARBONATE, CRUDE 12 [hp_X]/1 mL; STRYCHNOS IGNATII SEED 12 [hp_X]/1 mL; LYCOPODIUM CLAVATUM SPORE 12 [hp_X]/1 mL; SODIUM CHLORIDE 12 [hp_X]/1 mL; STRYCHNOS NUX-VOMICA SEED 12 [hp_X]/1 mL; PHOSPHORIC ACID 12 [hp_X]/1 mL; PHOSPHORUS 12 [hp_X]/1 mL; ZINC 12 [hp_X]/1 mL
INACTIVE INGREDIENTS: WATER; ALCOHOL

DRUG FACTS:

ACTIVE INGREDIENTS:

(in each drop) Arsenicum Iodatum 12X 9.07%, Calcarea Carbonica 12X 9.07%, Glandula Suprarenalis Suis 8X 9.07%, Hypothalamus Suis 8X 9.07%, Ignatia Amara 12X 9.07%, Lycopodium Clavatum 12X 9.07%, Natrum Muriaticum 12X 9.07%, Nux Vomica 12X 9.07%, Phosphorus 12X 9.07%, Phosphoricum Acidum 12X 9.07%, Zincum Metallicum 12X 9.07%, Aralia Quinquefolia 3X 0.10%, Avena Sativa 3X 0.10%

PURPOSE:

Arsenicum Iodatum - swelling,** Calcarea Carbonica - fatigue,** Glandula Suprarenalis Suis - apathy,** Hypothalamus Suis - sadness,** Ignatia Amara – low appetite,** Lycopodium Clavatum - Faintness,** Natrum Muriaticum – heat intolerance,** Nux Vomica – early waking,** Phosphorus - thirst,** Phosphoricum Acidum - disinterest,** Zincum Metallicum - restlessness,** Aralia Quinquefolia - drowsiness,** Avena Sativa – sleeplessness**

**Claims based on traditional homeopathic practice, not accepted medical evidence. Not FDA evaluated.

USES:

May temporarily relieve: • nervous exhaustion • fatigue • forgetfulness.**

**Claims based on traditional homeopathic practice, not accepted medical evidence. Not FDA evaluated.

WARNINGS:

Stop use and ask a doctor if symptoms persist for more than 7 days.

If pregnant or breastfeeding, ask a health professional before use.

Keep out of reach of children. In case of overdose, get medical help or contact a Poison Control Center right away.

DO NOT USE IF TAMPER EVIDENT SEAL IS BROKEN OR MISSING

Store in a cool, dry place.

KEEP OUT OF REACH OF CHILDREN:

In case of overdose, get medical help or contact a Poison Control Center right away.

DIRECTIONS:

• Adults and children 5 to 10 drops orally, 3 times daily or as otherwise directed by a health care professional.

• Consult a physician for use in children under 12 years of age.

INACTIVE INGREDIENTS:

Demineralized water, 20% Ethanol.

QUESTIONS:

Dist. by Energique, Inc.

201 Apple Blvd

Woodbine, IA 51579

800.869.8078

PACKAGE LABEL DISPLAY:

ENERGIQUE

SINCE 1987

HOMEOPATHIC REMEDY

ADRENAPAR

1 fl. oz. (30 ml)